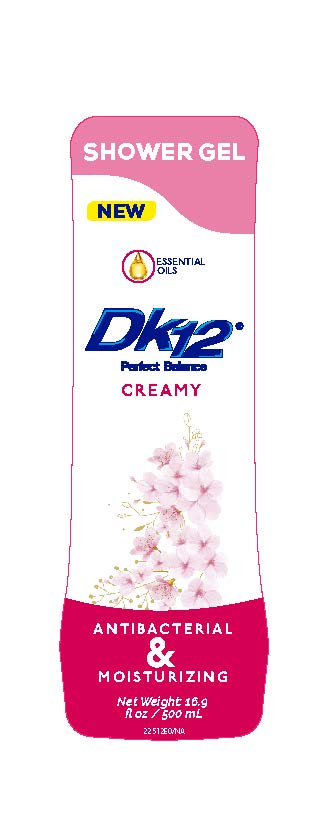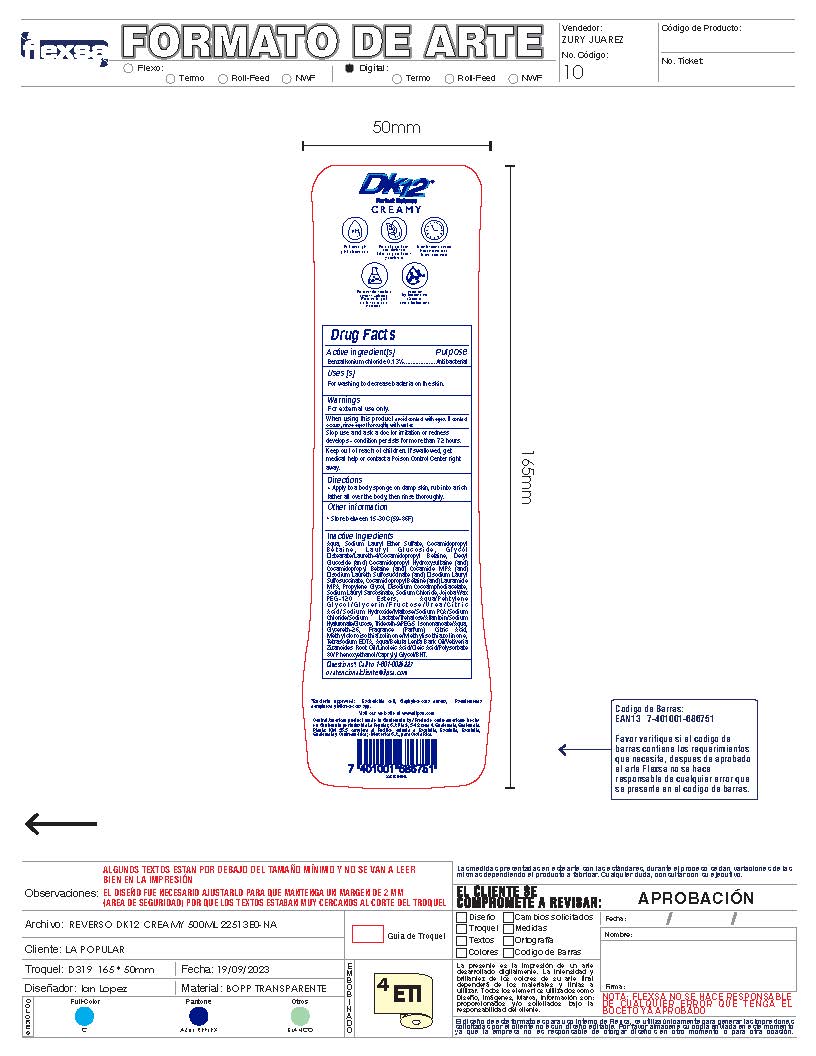 DRUG LABEL: DK12 Shower Gel Creamy
NDC: 62476-010 | Form: GEL
Manufacturer: Industria La Popular, S.A.
Category: otc | Type: HUMAN OTC DRUG LABEL
Date: 20241202

ACTIVE INGREDIENTS: BENZALKONIUM CHLORIDE 0.65 g/500 mL
INACTIVE INGREDIENTS: ALLANTOIN; MALTOSE; GLYCERETH-26; COCAMIDOPROPYL BETAINE; LAURAMIDE; DECYL GLUCOSIDE; COCAMIDOPROPYL HYDROXYSULTAINE; HYDROLYZED JOJOBA ESTERS (ACID FORM); DISODIUM LAURYL SULFOSUCCINATE; SODIUM LAURYL SARCOSINATE; SODIUM CHLORIDE; LAURYL GLUCOSIDE; UREA; TREHALOSE; LAURETH-4; COCAMIDE; METHYLCHLOROISOTHIAZOLINONE; SODIUM LAURYL SULFATE; WATER; GLYCERIN; METHYLISOTHIAZOLINONE; ANHYDROUS CITRIC ACID; GLYCOL DISTEARATE; PHENOXYETHANOL; HYALURONATE SODIUM; EDETATE SODIUM; PROPYLENE GLYCOL; DISODIUM COCOAMPHODIACETATE; BETULA LENTA BARK; POLYSORBATE 80; BUTYLATED HYDROXYTOLUENE; PENTYLENE GLYCOL; SODIUM HYDROXIDE; SODIUM LACTATE; SODIUM PIDOLATE; ANHYDROUS DEXTROSE; DISODIUM LAURETH SULFOSUCCINATE; FRUCTOSE; LINOLEIC ACID; OLEIC ACID; CAPRYLYL GLYCOL; ISONONYL ISONONANOATE; TRIDECETH-9; VETIVERIA ZIZANIOIDES ROOT

DK12 Shower Gel Creamy

Active Ingredient

Benzalkonium Chloride 0.13%

Purpose

Antibacterial

Uses

For washing to decrease bacteria on the skin

Warnings

For External Use only.

When using this product

avoid contact with eyes. If contact occurs, rinse eyes thoroughly with water.

Stop use and ask a doctor

irritation or redness develops - condition persists for more than 72 hours.

Keep out of reach of children.

If swallowed, get medical help or contact a Poison Control Center right away

Directions

Apply to a body sponge on damp skin, rub into a rich lather all over the body, then rinse thoroughly.

Other Information

Store between 15-30C (59-86F)

Inactive Ingredients

Aqua, Sodium Lauryl Ether Sulfate, Cocamidopropyl B e t a i n e , L a u r y l G l u c o s i d e , G l y c o l
Distearate/Laureth-4/Cocamidopropyl Betaine, Decyl Glucoside (and) Cocamidopropyl Hydroxysultaine (and) Cocamidopropyl Betaine (and) Cocamide MIPA (and) Disodium Laureth Sulfosuccinate (and) Disodium Lauryl Sulfosuccinate, Cocamidopropyl Betaine (and) Lauramide MIPA, Propylene Glycol, Disodium Cocoamphodiacetate, Sodium Lauryl Sarcosinate, Sodium Chloride, Jojoba Wax PEG-120 Esters, Aqua/Pentylene G l y c o l / G l y c e r i n / F r u c t o s e / U r e a / C i t r i c Acid/Sodium Hydroxide/Maltose/Sodium PCA/Sodium Chloride/Sodium Lactate/Trehalose/Allantoin/Sodium Hyaluronate/Glucose, Trideceth-9/PEG-5 Isononanoate/Aqua, Glycereth-26, Fragrance (Parfum), Citric Acid, Methylcloroisothiazolinone/Methylisothiazolinone, Tetrasodium EDTA, Aqua/Betula Lenta Bark Oil/Vetiveria Zizanoides Root Oil/Linoleic Acid/Oleic Acid/Polysorbate 80/ Phenoxyethanol/Caprylyl Glycol/BHT.